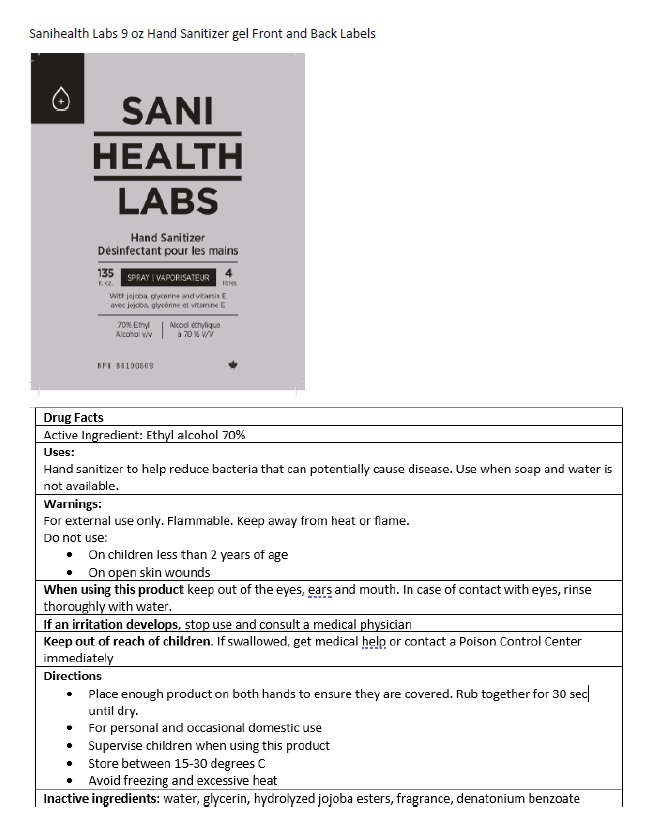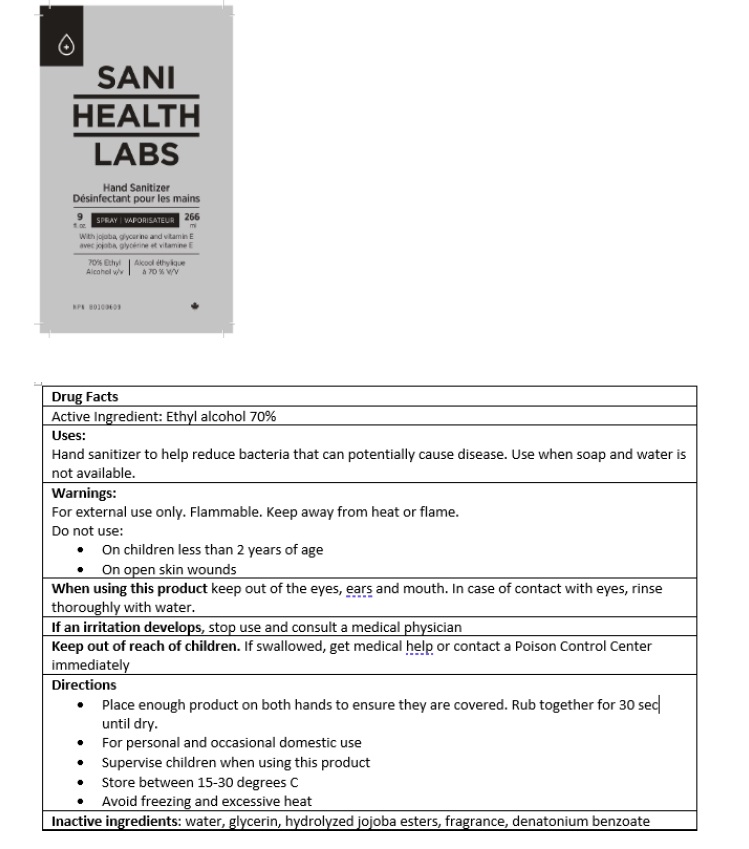 DRUG LABEL: SaniHealth Labs Hand Sanitizer
NDC: 79861-001 | Form: LIQUID
Manufacturer: Sanihealth Labs Inc.
Category: otc | Type: HUMAN OTC DRUG LABEL
Date: 20200822

ACTIVE INGREDIENTS: ALCOHOL 0.7 mL/1 mL
INACTIVE INGREDIENTS: WATER; DENATONIUM BENZOATE; HYDROLYZED JOJOBA ESTERS (ACID FORM); GLYCERIN

SaniHealth Labs Hand Sanitizer

Active Ingredients

Ethyl Alcohol 70%v/v.

Purpose: Antiseptic

Purpose

Antiseptic

Safety Instructions

Flammable, Keep away from fire and flame

Ask Doctor

Stop Use and Ask a doctor if irritation or redness develops

KEEP OUT OF REACH OF CHILDREN

If swallowed, get medical help or contact Poison Control right away

Other Information

Store below 15-30°C
May discolor certain fabrics or surfaces.

Avoid freezing and excessive heat

Inactive Ingredients

water, hydrolyzed jojoba esters, glycerin, fragrance, denatonium benozate

Directions

- Place enough product in your palm to thoroughly cover your hands
- Rub hands together briskly until dry
- Children should be supervised when using this product.
- For personal and occasional domestic use

Warnings

For external use only.

Flammable. Keep away from fire or flame.

Uses

- helps reduce bacteria on the skin that could cause disease